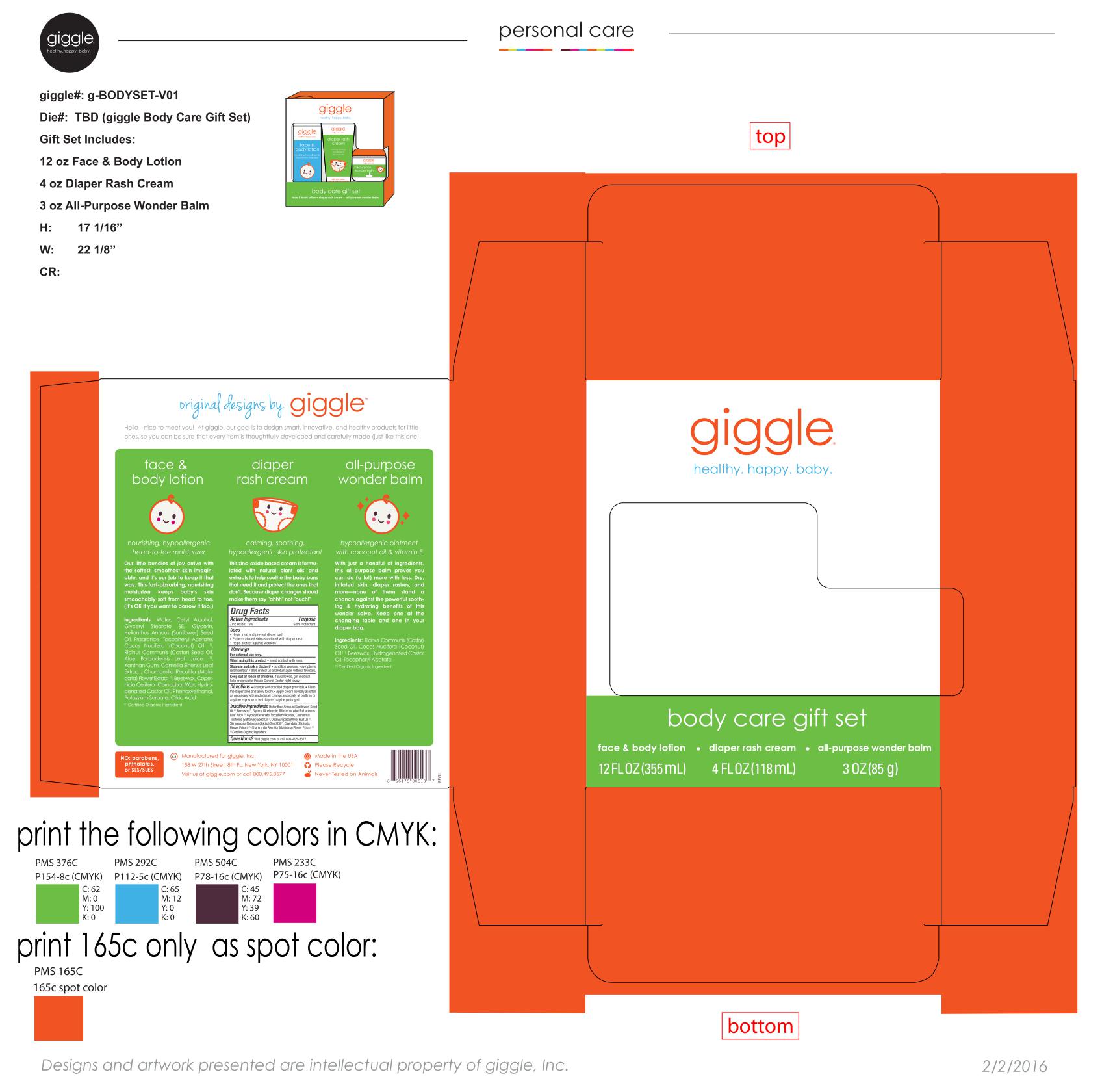 DRUG LABEL: body care gift set
NDC: 70306-9804 | Form: KIT | Route: TOPICAL
Manufacturer: giggle
Category: otc | Type: HUMAN OTC DRUG LABEL
Date: 20160218

ACTIVE INGREDIENTS: ZINC OXIDE 19 g/100 mL
INACTIVE INGREDIENTS: CHAMOMILE; GLYCERYL MONOBEHENATE; ALPHA-TOCOPHEROL ACETATE; JOJOBA OIL; YELLOW WAX; GLYCERYL DIBEHENATE; SAFFLOWER OIL; OLIVE OIL; ALOE VERA LEAF; CALENDULA OFFICINALIS FLOWER; SUNFLOWER OIL; TRIBEHENIN

Kit containing diaper rash cream for 2016

Active Ingredients

Zinc Oxide: 19%

Purpose

Skin Protectant

Uses

* Helps treat and prevent diaper rash
* Protects chafed skin associated with diaper rash
* Helps protect against wetness

Warnings

For external use only.

When using this product * avoid contact with eyes.

Stop use and ask a doctor if * condition worsens * symptoms last more than 7 days or clear up and return again within a few days.

Keep out of reach of children. If swallowed, get medical help or contact a Poison Control Center right away.

Directions

* Change wet or soiled diaper promptly. * Cleanse the diaper area and allow to dry. * Apply cream liberally as often as necessary, with each diaper change, especially at bedtime or anytime exposure to wet diapers may be prolonged.

Inactive Ingredients

Helianthus Annuus (Sunflower) Seed Oil(1), Beeswax(1), Glyceryl Dibehenate, Tribehenin, Aloe Barbadensis Leaf Juice(1), Glyceryl Behenate, Tocopheryl Acetate, Carthamus Tinctorius (Safflower) Seed Oil(1), Olea Europae (Olive) Fruite Oil(1), Simmondsia Chinensis (Jojoba) Seed Oil(1), Calendula Officialis Flower Extract(1), Chamomilla Recutita (Matricaria) Flower Extract(1)(1) Certified Organic Ingredient

Questions?

Questions? Visit giggle.com or call 800-495-8577